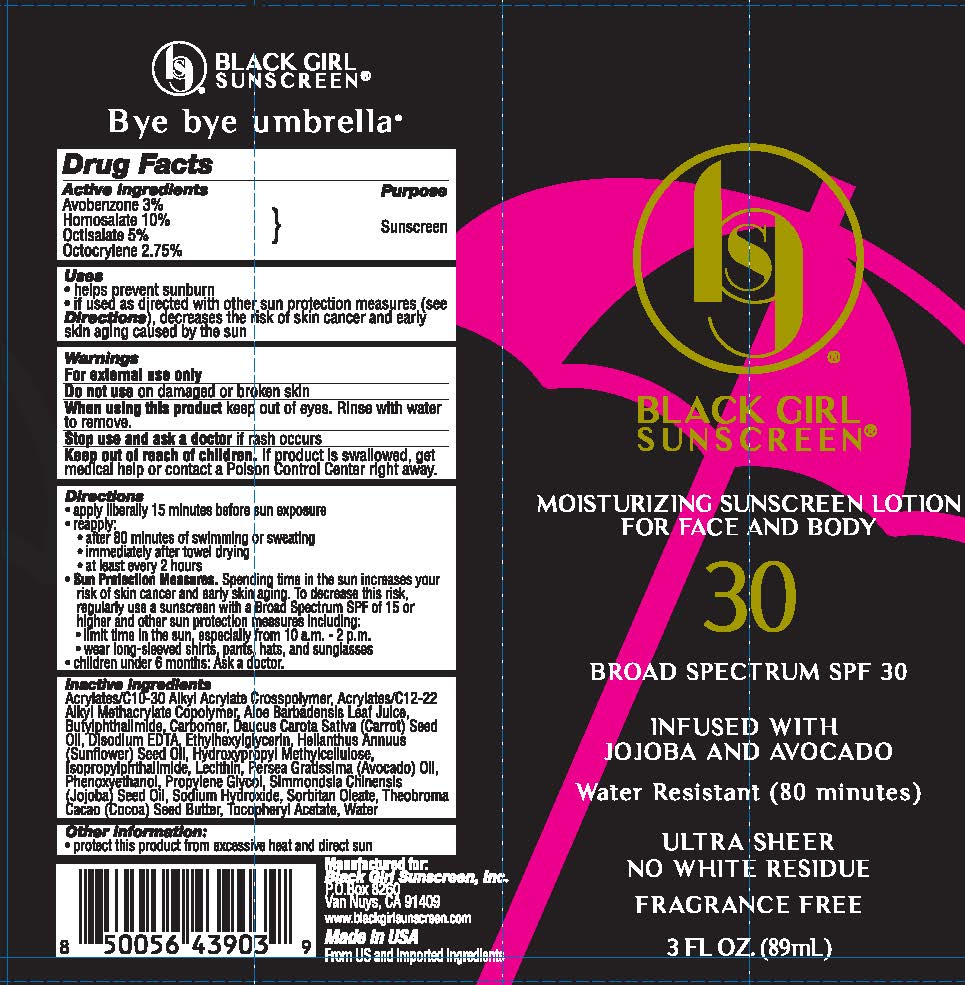 DRUG LABEL: Black Girl Sunscreen
NDC: 84204-0012 | Form: LOTION
Manufacturer: Black Girl Sunscreen, LLC
Category: otc | Type: HUMAN OTC DRUG LABEL
Date: 20250115

ACTIVE INGREDIENTS: AVOBENZONE 29.4 mg/1 mL; HOMOSALATE 98 mg/1 mL; OCTISALATE 49 mg/1 mL; OCTOCRYLENE 26.95 mg/1 mL
INACTIVE INGREDIENTS: HELIANTHUS ANNUUS (SUNFLOWER) SEED OIL; ACRYLATES/C10-30 ALKYL ACRYLATE CROSSPOLYMER (60000 MPA.S); AVOCADO OIL; ALOE VERA LEAF; EDETATE DISODIUM; LECITHIN, SOYBEAN; PHENOXYETHANOL; COCOA BUTTER; CARROT SEED OIL; ETHYLHEXYLGLYCERIN; WATER; PROPYLENE GLYCOL; ISOPROPYLPHTHALIMIDE; CARBOMER HOMOPOLYMER TYPE C; HYPROMELLOSES; JOJOBA OIL; SORBITAN MONOOLEATE; .ALPHA.-TOCOPHEROL ACETATE; N-BUTYLPHTHALIMIDE; SODIUM HYDROXIDE

Black Girl Sunscreen Broad Spectrum SPF 30 Ultra Sheer Lotion

Active Ingredients

Avobenzone 3%

Homosalate 10%

Octisalate 5%

Octocrylene 2.75%

Purpose

Sunscreen

Uses

- helps prevent sunburn
- if used as directed with other sun protection measures (see Directions), decreses the risk of skin cancer and early skin aging caused by the sun

Warnings

For external use only

Do not useon damaged or broken skin

WHEN USING

When using this productkeep out of eyes. Rinse with water to remove.

Stop use and ask a doctorif rash occurs

Keep out of reach of children.If product is swallowed, get medical help or contact a Poison Control Center right away.

Directions

- apply liberally 15 minutes before sun exposure
- reapply
- after 80 minutes of swimming or sweating
- inmediately after towel drying
- at least every 2 hours
- Sun Protection Measures.Spending time in the sun increases your risk of skin cancer and early skin aging. To decrease this risk, regularly use a sunscreen with a Broad Spectrum SPF of 15 or higher and other sun protection measures, including:
- limit time in the sun, specially from 10 a.m. - 2 p.m.
- wear long-sleeve shirts, pants, hats & sunglasses.
- children under 6 months: Ask a doctor.

Inactive ingredients

Acrylates/C10-30 Alkyl Acrylate Crosspolymer, Acrylates/C12-22 Alkyl Methacrylate Copolymer, Aloe Barbadensis Leaf Juice, Butylphthalimide, Carbomer, Daucus Carota Sativa (Carrot) Seed Oil, Disodium EDTA, Ethylhexylglycerin, Helianthus Annuus (Sunflower) Seed Oil, Hydroxypropyl Methylcellulose, Isopropylphthalimide, Lecithin, Persea Gratissima (Avocado) Oil, Phenoxyethanol, Propylene Glycol, Simmondsia Chinensis (Jojoba) Seed Oil, Sodium Hydroxide, Sorbitan Oleate, Theobroma Cacao (Cocoa) Seed Butter, Tocopheryl Acetate, Water

Other Information

- protect this product from excessive heat and direct sun